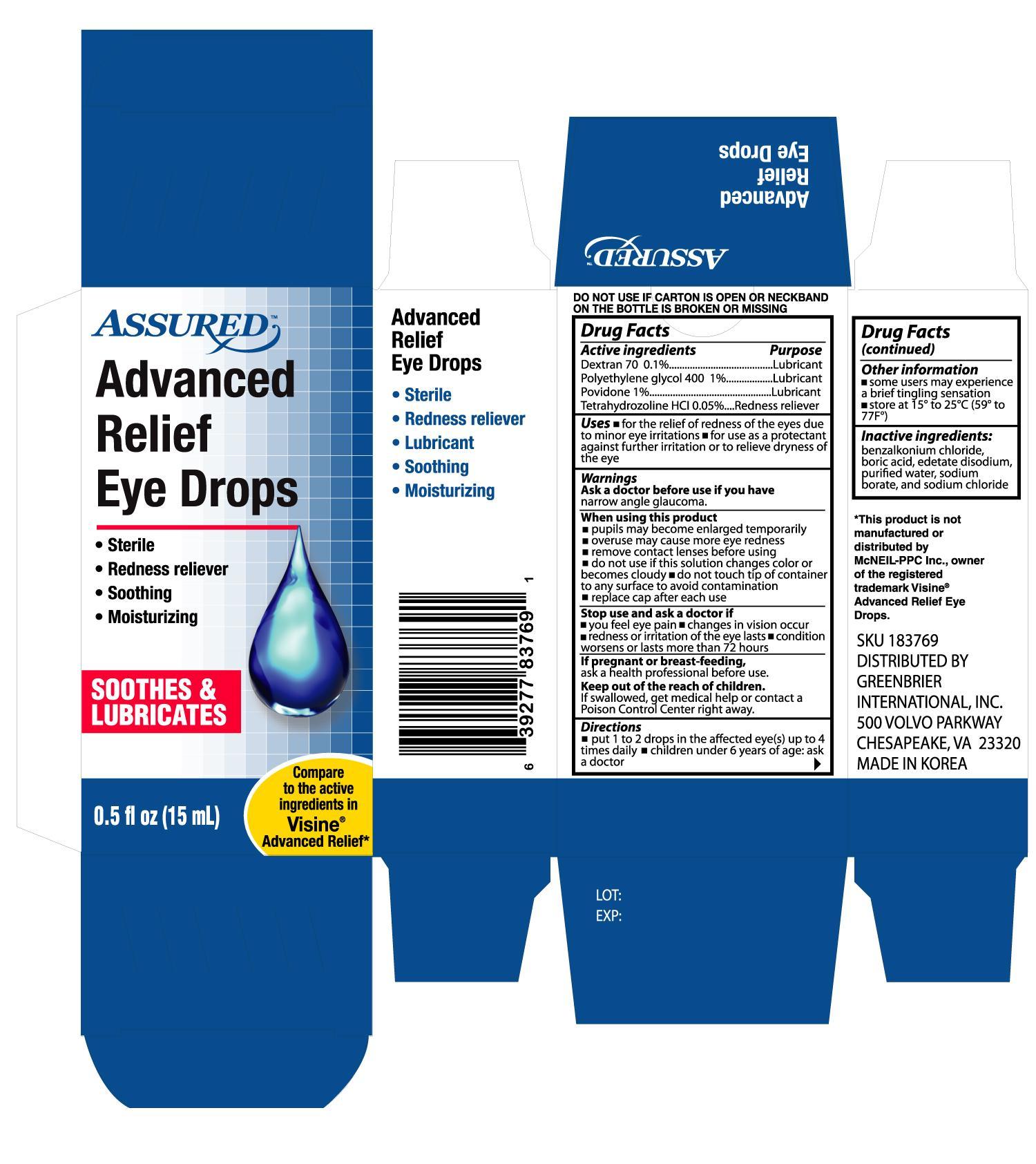 DRUG LABEL: ASSURED ADVANCED RELIEF EYE
NDC: 33992-8376 | Form: SOLUTION
Manufacturer: GREENBRIER INTERNATIONAL, INC.
Category: otc | Type: HUMAN OTC DRUG LABEL
Date: 20130228

ACTIVE INGREDIENTS: DEXTRAN 70 1 mg/1 mL; POLYETHYLENE GLYCOL 400 10 mg/1 mL; POVIDONE 10 mg/1 mL; TETRAHYDROZOLINE HYDROCHLORIDE 0.5 mg/1 mL
INACTIVE INGREDIENTS: BENZALKONIUM CHLORIDE; BORIC ACID; EDETATE DISODIUM; SODIUM CHLORIDE; SODIUM BORATE; WATER

Drug Facts

Active ingredients Purpose

Dextran 70 0.1%..........................................................Lubricant

Polyethylene Glycol 400 1% ........................................Lubricant

Povidone 1% ..............................................................Lubricant

Tetrahydrozoline HCL 0.05% .......................................Redness reliever

Uses

- for the relief of redness of the eyes due to minor eye irritations
- for use as a protectant against further irritation or to relieve dryness of the eye

Ask a doctor before use if you have narrow angle glaucoma

When using this product

- pupils may become enlarged temporarily
- overuse may cause more eye redness
- remove contact lenses before using
- do not use if this solution changes color or becomes cloudy
- do not touch tip of container to any surface to avoid contamination
- replace cap after each use

Stop use and ask a doctor if

- you feel eye pain
- changes in vision occur
- redness or irritation of the eye lasts
- condition worsens or lasts more than 72 hours

PREGNANCY OR BREAST FEEDING

If pregnant or breast-feeding, ask a health professional before use.

Keep out of the reach of children.

If swallowed, get medical help or contact a Poison Control Center right away.

Directions

- put 1 to 2 drops in the affected eye(s) up to 4 times daily
- children under 6 years of age: ask a doctor

Other information

- some users may experience a brief tingling sensation
- store at 15o to 25oC (59o to 77oF)

INACTIVE INGREDIENT

Inactive ingredients: benzalkonium chloride, boric acid, edetate disodium, purified water, sodium chloride, and sodium borate

DOSAGE AND ADMINISTRATION

DISTRIBUTED BY:

GREENBRIER INTERNATIONAL, INC.

500 VOLVO PARKWAY

CHESAPEAKE, VA 23320

MADE IN KOREA